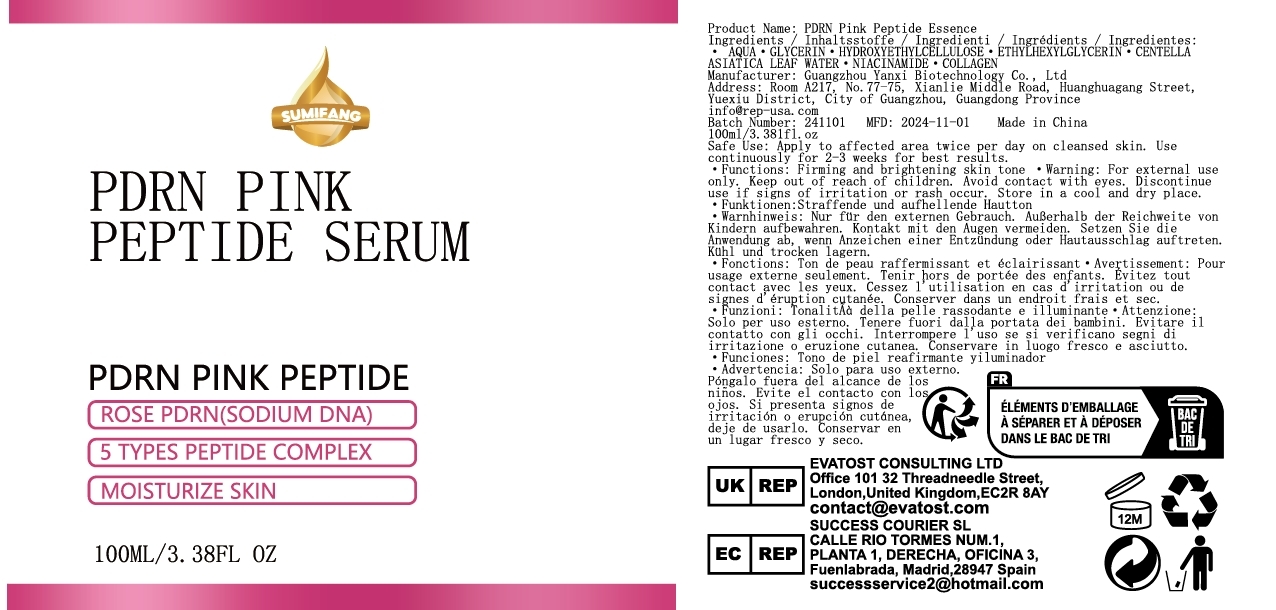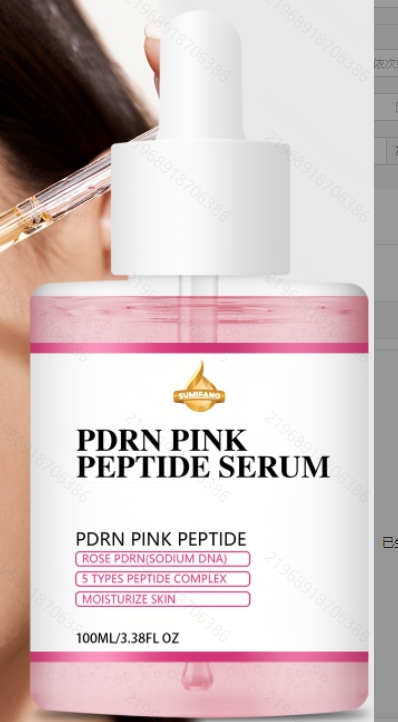 DRUG LABEL: PDRN Pink Peptide Essence
NDC: 84025-293 | Form: LIQUID
Manufacturer: Guangzhou Yanxi Biotechnology Co., Ltd
Category: otc | Type: HUMAN OTC DRUG LABEL
Date: 20241220

ACTIVE INGREDIENTS: HYDROXYETHYLCELLULOSE 3 mg/100 mL; GLYCERIN 5 mg/100 mL
INACTIVE INGREDIENTS: WATER

DOSAGE AND ADMINISTRATION

Apply to affected area twice per day on cleansed skin. Use continuously for 2-3 weeks for best results.

WARNINGS

Keep out of children

INACTIVE INGREDIENT

Aqua

INDICATIONS AND USAGE

for daily face care

keep out of children

PURPOSE

Firm up and hydrate your face